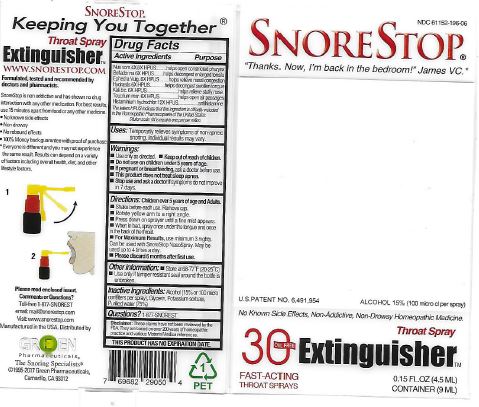 DRUG LABEL: Snore Stop Extinguisher Throat
NDC: 61152-196 | Form: SPRAY
Manufacturer: Green Pharmaceuticals
Category: homeopathic | Type: HUMAN OTC DRUG LABEL
Date: 20181219

ACTIVE INGREDIENTS: ATROPA BELLADONNA 6 [hp_X]/4.5 mL; EPHEDRA DISTACHYA FLOWERING TWIG 6 [hp_X]/4.5 mL; HISTAMINE DIHYDROCHLORIDE 12 [hp_X]/4.5 mL; GOLDENSEAL 6 [hp_X]/4.5 mL; POTASSIUM DICHROMATE 6 [hp_X]/4.5 mL; STRYCHNOS NUX-VOMICA SEED 6 [hp_X]/4.5 mL; TEUCRIUM MARUM 6 [hp_X]/4.5 mL
INACTIVE INGREDIENTS: ALCOHOL; GLYCERIN; POTASSIUM SORBATE; WATER

Snore Stop Extinguisher Throat Spray 30 Fast-Acting Throat Spray

Active Ingredients (HPUS) Purpose

Nux vom. 4X, 6X, HPUS....helps open constricted pharynx

Belladonna 6X HPUS....helps decongest enlarged tonsils

Ephedra Vulg. 6X HPUS....helps relieve nasal congestion

Hydrastis 6X HPUS....helps decongest swollen tongue

Kali bic. 6X HPUS....helps relieve stuffy nose

Teucrium mar. 6X HPUS....helps open air passages

Histaminium hydrochlor 12X HPUS....antihistamine

The letters HPUS indicate that this ingredient is officially included in the Homeopathic Pharmacopoeia of the United States.

Dilution scale: 6X is equal to one part million.

Inactive Ingredients:

Alcohol (100 micro centiliters per spray), Glycerin, Potassium sorbate, Purified water (75%).

Warnings:

- Use only as directed.
- Keep out of reach of children.
- Do not use on children under 5 years of age.
- If pregnant or breastfeeding, ask a doctor before use.
- This product does not treat sleep apnea.
- Stop use and ask a doctor if symptoms do not improve in 7 days.

Directions: Children over 5 year of age and Adults.

- Shake before each use. Remove cap.
- Rotate yellow arm to a right angle.
- Press down on sprayer until a fine mist apprears.
- When in bed, spray once under the tongue and once in the back of the throat.
- For Maximum Results, use minimum 3 nights.

Can be used with SnoreStop NasoSpray. May be used up to 4 times a day.

- Please discard 6 months after first use.

Dosage and Administration:

Directions: Children over 5 years of age and Adults.

- Shake before each use. Remove cap.
- Rotate yellow arm to a right angle.
- Press down on sprayer until fine mist appears.
- When in bed, spray once under the tongue and once in the back of the throat.
- For Maximum Results, use minimum 3 nights.

Can be used with SnoreStop NasoSpray. May be used up to 4 time a day.

- Please discard 6 months after first use.

Uses:

Temporarily relieves symptoms on non-apneic snoring. Individual results may vary.

Keep out of reach of children.

Other information:

- Store at 68-77°F (20-25°C)
- Use only if tamper resistant seal around the bottle is unbroken.